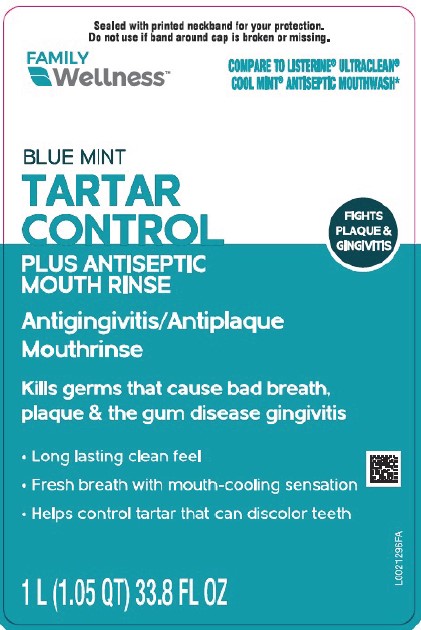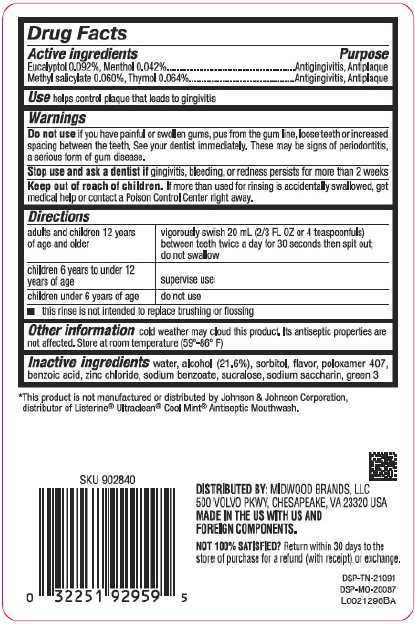 DRUG LABEL: Tartar control
NDC: 55319-585 | Form: MOUTHWASH
Manufacturer: Family Dollar Stores, Inc
Category: otc | Type: HUMAN OTC DRUG LABEL
Date: 20260224

ACTIVE INGREDIENTS: THYMOL 0.64 mg/1 mL; EUCALYPTOL 0.92 mg/1 mL; MENTHOL 0.42 mg/1 mL; METHYL SALICYLATE 0.6 mg/1 mL
INACTIVE INGREDIENTS: WATER; ALCOHOL; SORBITOL; POLOXAMER 407; BENZOIC ACID; ZINC CHLORIDE; SODIUM BENZOATE; SUCRALOSE; SACCHARIN SODIUM; FD&C GREEN NO. 3

Family Wellness 855.000/855AA-AC
Tartar Control Plus Antiseptic Mouth Rinse, Blue Mint

Active ingredients

Eucalyptol 0.092%

Menthol 0.042%

Methyl salicylate 0.060%

Thymol 0.064%

Purpose

Antigingivitis, Antiplaque

Use

helps control plaque that leads to gingivitis

Warnings

for this product

Do not use

if you have painful or swollen gums, pus from the gum line, loose teeth or increased spacing between the teeth. See your dentist immediately. These may be signs of periodontitis, a serious form of gum disease.

Stop use and ask a dentist if

gingivitis, bleeding, or redness persists for more than 2 weeks.

Keep out of reach of children.

If more than used for rinsing is accidentally swallowed, get medical help or contact a Poison Control Center right away.

Directions

adults and children 12 years of age and older - vigorously swish 20 mL (2/3 FL OZ or 4 teaspoonfuls) between teeth twice a day for 30 seconds then spit out; do not swallow

children 6 years to under 12 years of age - supervise use

children under 6 yeard of age - do not use

- this rinse is not intended to replace brushing or flossing

Other information

cold weather may cloud this product. Its antiseptic properties are not affected. Store at room temperature (59°-86°F)

Inactive ingredients

water, alcohol (21.6%), sorbitol, flavor, poloxamer 407, benzoic acid, zinc chloride, sodium benzoate, sucralose, sodium saccharin, green 3

Disclaimer

*This product is not manufactured or distributed by Johnson & Johnson Corporation, distributor of Listerine®Ultraclean®Cool MintAntiseptic Mouthwash*

Adverse Reactions

DISTRIBUTED BY: MIDWOOD BRANDS, LLC

500 VOLVO PKWY, CHESAPEAKE, VA 23320 USA

MADE IN THE US WITH US AND FOREIGN COMPONENTS.

NOT 100% SATISFIED? Return within 30 days to the store of purchase for a refund (with receipt) or exchange.

DSP-TN-21091

DSP-MO-20087

Principal display panel

Sealed with printed neckband for your protection.

Do not use if band around cap is broken or missing.

FAMILY WELLNESS™

Compare TO LISTERINE® ULTRACLEAN® COOL MINT® ANTISEPTIC MOUTHWASH*

BLUE MINT

TARTAR CONTROL

PLUS ANTISEPTIC

MOUTHRINSE

ANTIGINGIVITIS/ANTIPLAQUE

Kills germs that cause bad breath, plaque & the gum disease gingivitis

- Long lasting clean feel
- Fresh breath with mouth-cooling sensation
- Helps control tartar that can discolor teeth

FIGHTS PLAQUE & GINGIVITIS

1 L (1.05 QT) 33.8 FL OZ